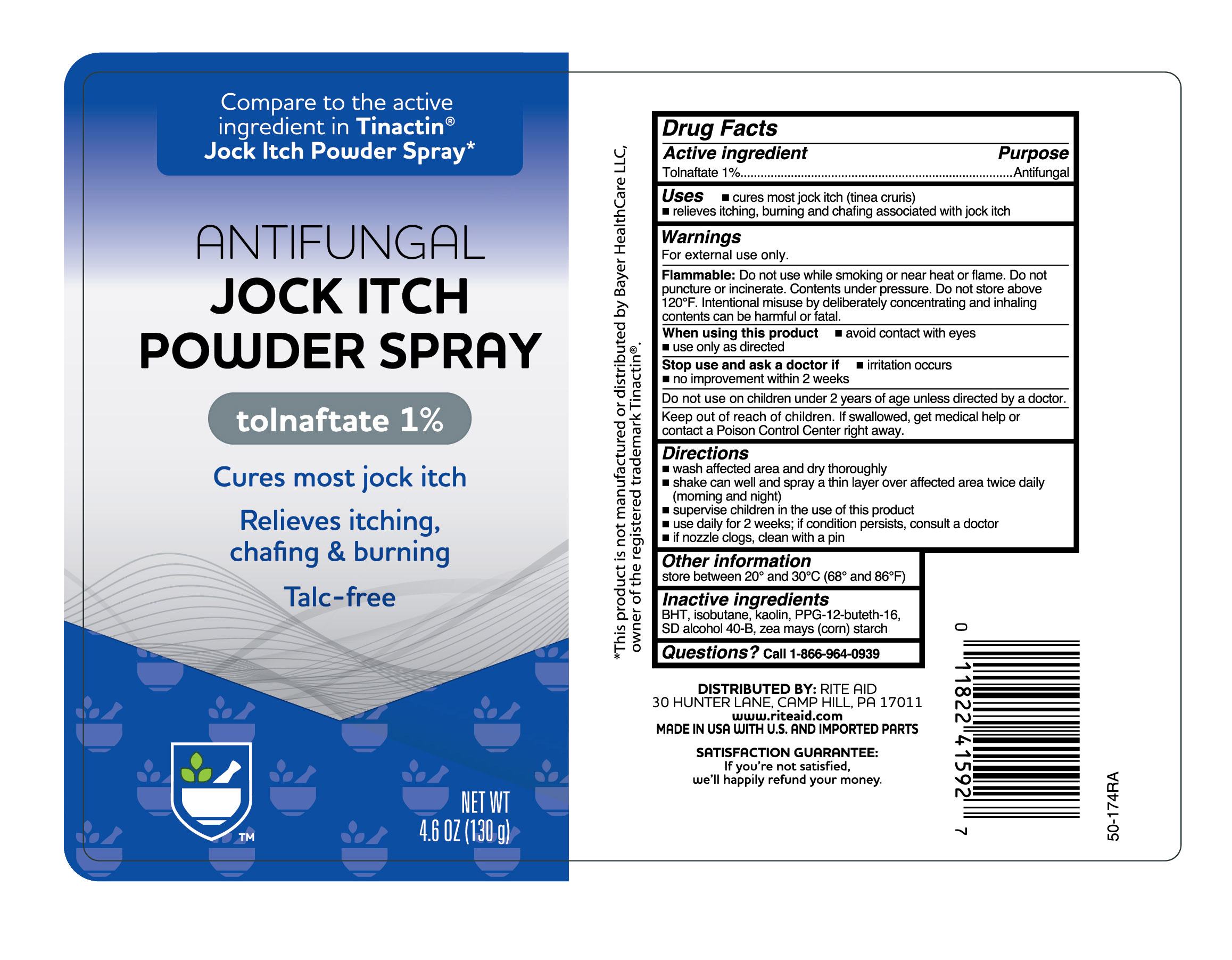 DRUG LABEL: Tolnaftate
NDC: 11822-0782 | Form: AEROSOL, SPRAY
Manufacturer: Rite Aid Corporation
Category: otc | Type: HUMAN OTC DRUG LABEL
Date: 20250621

ACTIVE INGREDIENTS: TOLNAFTATE 1.3 g/130 g
INACTIVE INGREDIENTS: KAOLIN; BUTYLATED HYDROXYTOLUENE; ISOBUTANE; PPG-12-BUTETH-16; ALCOHOL; ZEA MAYS SUBSP. MAYS WHOLE

Rite Aid Antifungal Jock Itch Powder Spray Tolnaftate 1%

Active ingredient

Tolnaftate 1%

Purpose

Antifungal

Uses

- cures most jock itch (tinea cruris)
- relieves itching, burning and chafing associated with jock itch

Warnings

For external use only.

Flammable:

Do not use while smoking or near heat or flame. Do not puncture or incinerate. Contents under pressure. Do not store above 120ºF. Intentional misuse by deliberately concentrating and inhaling contents can be harmful or fatal.

When using this product

- avoid contact with eyes
- use only as directed

Stop use and ask a doctor if

- irritation occurs
- no improvement within 2 weeks

Do not use

- on children under 2 years of age unless directed by a doctor.

Keep out of reach of children.

If swallowed, get medical help or contact a Poison Control Center right away.

Directions

- wash affected area and dry thoroughly
- shake can well and spray a thin layer over affected area twice daily (morning and night)
- supervise children in the use of this product
- use daily for 2 weeks; if conditions persists, consult a doctor
- if nozzle clogs, clean with a pin

Other information

store between 20º and 30ºC (68º and 86ºF)

Inactive ingredient

BHT, isobutane, kaolin, PPG-12-buteth-16, SD alcohol 40-B, zea mays (corn) starch

Questions?

Call 1-866-964-0939

Principal Display Panel

Compare to the active

ingredient, in Tinactin

Jock Itch Powder Spray

ANTIFUNGAL

JOCK ITCH

POWDER SPRAY

tolnaftate 1%

Cures most jock itch
Relieves itching, chafing & burning
Talc-free

NET WT

4.6 OZ (130 g)